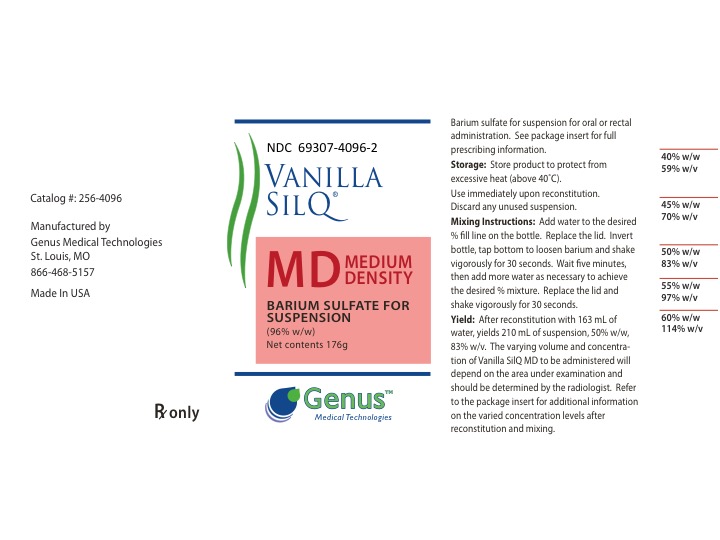 DRUG LABEL: Vanilla SilQ MD
NDC: 69307-4096 | Form: POWDER, FOR SUSPENSION
Manufacturer: Genus Medical Technologies, LLC
Category: prescription | Type: HUMAN PRESCRIPTION DRUG LABEL
Date: 20210111

ACTIVE INGREDIENTS: Barium Sulfate 96 g/100 g

Vanilla SilQ MD(R)

DESCRIPTION

VANILLA SILQ MD™ is a barium sulfate for suspension 96% w/w for oral and rectal administration. Each 100 g contains 96 g barium sulfate. Barium sulfate, due to its high molecular density is opaque to x-rays and therefore, acts as a positive contrast agent for radiographic studies. The active ingredient is barium sulfate and its structural formula is BaSO4. Barium sulfate occurs as a fine, white, odorless, tasteless, bulky powder which is free from grittiness. Its aqueous suspensions are neutral to litmus. It is practically insoluble in water, solutions of acids and alkalies, and organic solvents.

Inactive Ingredients

simethicone, sorbitol, saccharin sodium, natural and artificial flavor, emulsifers, and thickening agents

CLINICAL PHARMACOLOGY

Barium sulfate, due to its high molecular density is opaque to x-rays and, therefore, acts as a positive contrast agent for radiographic studies. Barium sulfate is biologically inert and, therefore, is not absorbed or metabolized by the body, and is eliminated from the GI tract unchanged. Excretion rate is a function of gastrointestinal transit time.

INDICATIONS AND USAGE

For use as a contrast agent in radiographic studies.

CONTRAINDICATIONS

This product should not be used in patients with known or suspected gastric or intestinal perforation, patients with conditions that may increase the risk of perforation; hypersensitivity to barium sulfate products; suspected tracheoesophageal fistula; obstructing lesions of the small intestine; pyloric stenosis; inflammation or neoplastic lesions of the rectum; or in patients who have had a recent rectal biopsy.

Barium sulfate suspensions should not be used for infants with swallowing disorders or for newborns with complete duodenal or jejunal obstruction or when distal small bowel or colon obstruction is suspected. Barium sulfate suspension is not recommended for very small preterm infants and young babies requiring small volumes of contrast media or for infants and young children when there is a possibility of leakage from the gastrointestinal tract, such as nectrotizing enterocolitis, unexplained pneumoperitoneum, gasless abdomen, other bowel perforation, esophageal perforation or post operative anastomosis.

WARNINGS

Serious adverse reactions, including death, have been reported with the administration of barium sulfate formulations and are usually associated with the technique of administration, the underlying pathological condition and / or patient hypersensitivities.

PRECAUTIONS

General: Procedures which involve the use of radiopaque contrast agents should be carried out under the direction of personnel with the requisite training and with a thorough knowledge of the particular procedure to be performed. A history of bronchial asthma, atopy, as evidenced by hay fever and eczema, or a previous reaction to a contrast agent, warrant special attention. Caution should be exercised with the use of radiopaque media in severly debilitated patients and in those with marked hypertension or advanced cardiac disease. Ingestion of barium is not recommended in patients with a history of food aspiration. Use caution if administering this product to patients in whom the integrity of the swallowing mechanism is unknown. If barium is aspirated into the larynx, further administration should be immediately discontinued. After any barium study of the GI tract, it may be important to rehydrate the patient as quickly as possible to prevent impaction of the barium. To prevent barium impaction in the colon, the use of mild laxatives such as milk of magnesia or lactulose following completion of the examination may also be required. These mild laxatives are recommended on a routine basis and in patients with a history of constipation unless clinically contraindicated.

Administration: Give careful consideration to the risks and benefits of the administration of a barium sulfate suspension to patients with possible gastrointestinal blockage. Take care to minimize the amount of barium allowed to flow proximal to the tissue affected with blockage or lesion. When administering this product with an enema tip, use caution to avoid insertion in a manner that is too forceful or deep, as this may cause tearing or perforation of the colorectal tissues.

Information for Patients:

Before using this product patients should be instructed to tell the physician ordering the procedure and the imaging technologist:

1. if they are pregnant.

2. if they are allergic to any foods or medication, or if they have had any prior reactions to barium sulfate products or other x-ray contrast agents.

3. if they are currently taking any medications, have any serious medical condition for which they are being treated or followed, or had any recent surgery.

Patients should seek immediate medical attention if they experience an allergic or other adverse reaction during or after use of this product.

Drug Interactions: The presence of barium sulfate formulations in the GI tract may alter the absorption of therapeutic agents taken concomitantly. In order to minimize any potential change in absorption, the separate administration of barium sulfate from that of other agents should be considered.

Usage in Pregnancy: Radiation is known to cause harm to the unborn fetus exposed in utero. Therefore, radiographic procedures should only be used when, in the judgment of the physician, its use is deemed essential to the welfare of the pregnant patient.

ADVERSE REACTIONS

Adverse reactions accompanying the use of barium sulfate formulations are infrequent and usually mild, though severe reactions (approximately 1 in 500,000) and fatalities (approximately 1 in 2,000,000) have occurred. Procedural complications are rare, but may include aspiration pneumonitis, barium sulfate impaction, granuloma formation, intravasation, embolization and peritonitis following intestinal perforation, vasovagal and syncopal episodes, and fatalities. EKG changes have been shown to occur following or during barium sulfate suspension enemas. It is of the utmost importance to be completely prepared to treat any such occurrence.

Due to the increased likelihood of allergic reactions in atopic patients, a complete history of known and suspected allergies as well as allergic-like symptoms, e.g. rhinitis, bronchial asthma, eczema and urticaria, must be obtained prior to any medical procedure.

Aspiration of large amounts of barium sulfate suspension may cause pneumonitis or nodular granulomas of interstitial lung tissues and lymph nodes; asphyxiation and death have been reported.

Transient bacteremia may occur during rectal administration of barium sulfate suspension, and septicemia has been reported.

A rare mild allergic reaction would most likely be generalized pruritis, erythema or urticaria (approximately 1 in 100,000 reactions). Such reactions will often respond to an antihistamine. More serious reactions (approximately 1 in 500,000) may result in laryngeal edema, bronchospasm or hypotension.

Severe reactions which may require emergency measures are often characterized by peripheral vasodilation, hypotension, reflex tachycardia, dyspnea, bronchospasm, agitation, confusion and cyanosis, progressing to unconsciousness. Treatment should be initiated immediately according to established standard of care.

Apprehensive patients may develop weakness, pallor, tinnitus, diaphoresis and bradycardia following the administration of any diagnostic agent. Such reactions are usually non-allergic in nature.

OVERDOSAGE

On rare occasions following repeated administrations, stomach cramps, nausea, vomiting, diarrhea or constipation may occur. Symptoms may be treated according to currently accepted standards of medical care.

DOSAGE AND ADMINISTRATION

Barium sulfate volume and method of administration are determined by individual technique, and may vary with differing patient and procedure characteristics. Add water to the desired % w/w fill line on bottle. Replace lid. Invert bottle, tap bottom to loosen barium, and shake vigorously for 30 seconds. Let stand at least 5 minutes. Add additional water as necessary to achieve the desired % mixture. Replace lid, and again shake vigorously for 30 seconds.

STORAGE

Store product to protect from excessive heat (above 40 degrees centigrade)